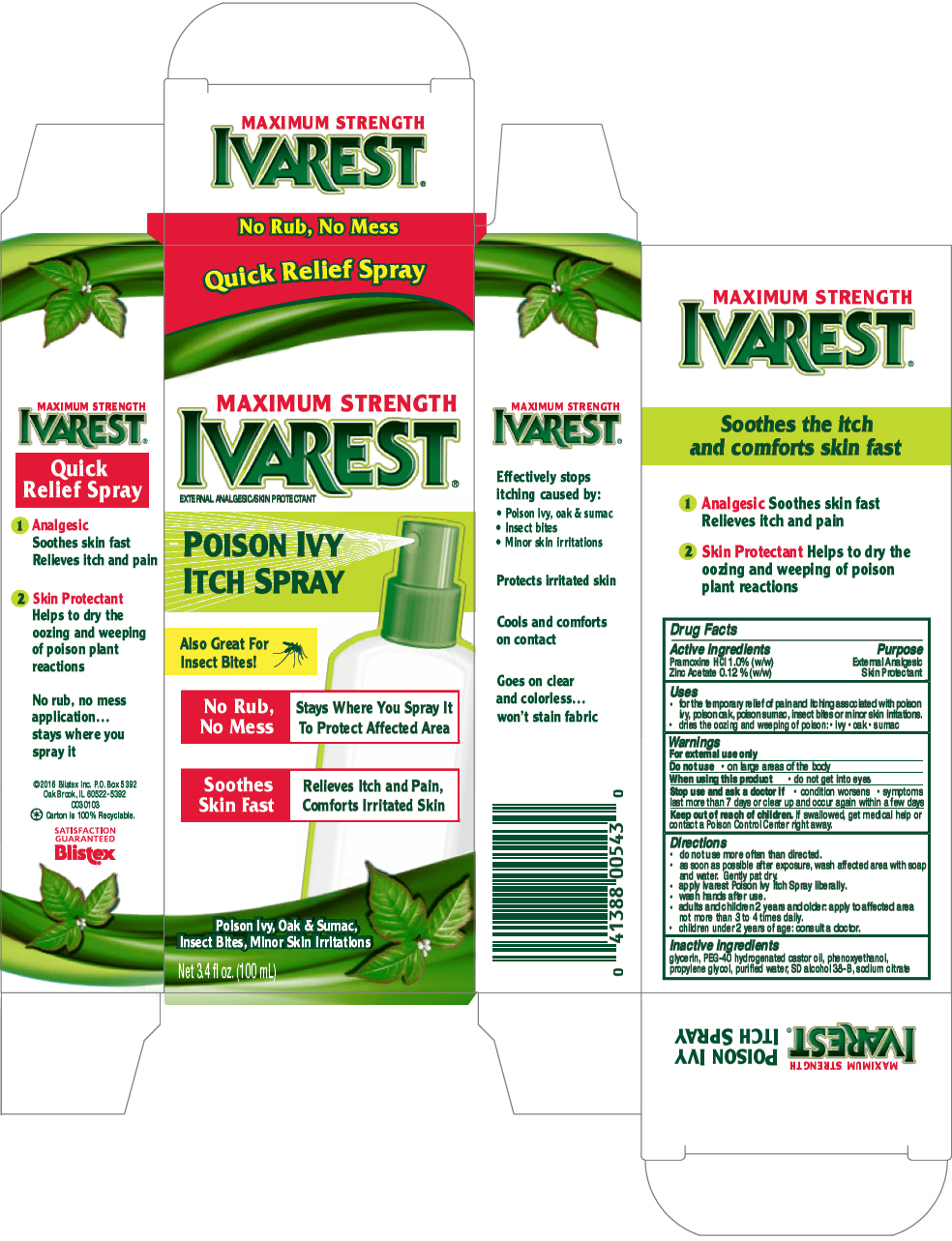 DRUG LABEL: Blistex Ivarest Poison Ivy Itch
NDC: 10157-2100 | Form: SPRAY
Manufacturer: Blistex Inc.
Category: otc | Type: HUMAN OTC DRUG LABEL
Date: 20241211

ACTIVE INGREDIENTS: Zinc Acetate 0.12 g/100 mL; PRAMOXINE HYDROCHLORIDE 1 g/100 mL
INACTIVE INGREDIENTS: WATER; ALCOHOL; Propylene Glycol; Glycerin; POLYOXYL 40 HYDROGENATED CASTOR OIL; Phenoxyethanol; SODIUM CITRATE, UNSPECIFIED FORM

Blistex Ivarest® Poison Ivy Itch Spray

Drug Facts

ACTIVE INGREDIENT

Active ingredients | Purpose
Pramoxine HCl 1.0% (w/w) | External Analgesic
Zinc Acetate 0.12 % (w/w) | Skin Protectant

Uses

- for the temporary relief of pain and itching associated with poison ivy, poison oak, poison sumac, insect bites or minor skin irritations.
- dries the oozing and weeping of poison:
  - ivy
  - oak
  - sumac

Warnings

For external use only

Do not use

- on large areas of the body

When using this product

- do not get into eyes

Stop use and ask a doctor if

- condition worsens
- symptoms last more than 7 days or clear up and occur again within a few days

Keep out of reach of children. If swallowed, get medical help or contact a Poison Control Center right away.

Directions

- do not use more often than directed.
- as soon as possible after exposure, wash affected area with soap and water. Gently pat dry.
- apply Ivarest Poison Ivy Itch Spray liberally.
- wash hands after use.
- adults and children 2 years and older: apply to affected area not more than 3 to 4 times daily.
- children under 2 years of age: consult a doctor.

Inactive ingredients

glycerin, PEG-40 hydrogenated castor oil, phenoxyethanol, propylene glycol, purified water, SD alcohol 38-B, sodium citrate

PRINCIPAL DISPLAY PANEL - 100 mL Bottle Carton

Quick Relief Spray

MAXIMUM STRENGTH
IVAREST®
EXTERNAL ANALGESIC/SKIN PROTECTANT

POISON IVY
ITCH SPRAY

Also Great For
Insect Bites!

No Rub,
No Mess
Stays Where You Spray It
To Protect Affected Area

Soothes
Skin Fast
Relieves Itch and Pain,
Comforts Irritated Skin

Poison Ivy, Oak & Sumac,
Insect Bites, Minor Skin Irritations

Net 3.4 fl oz. (100 mL)